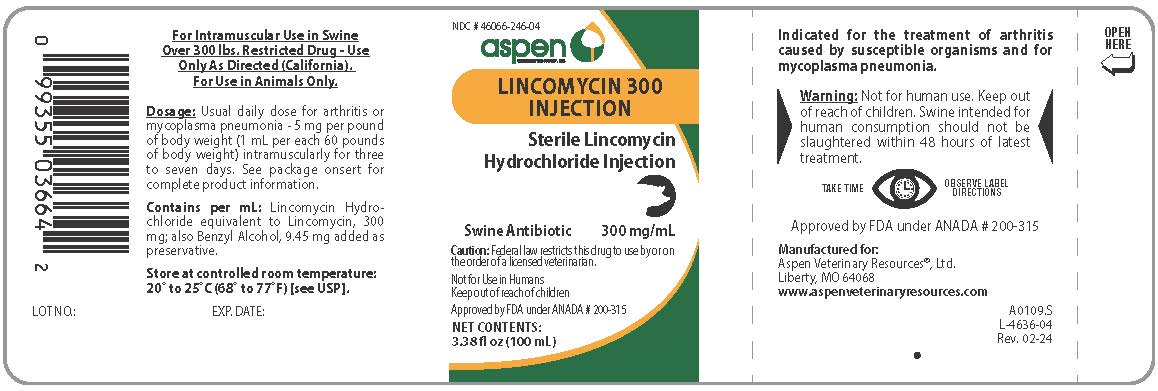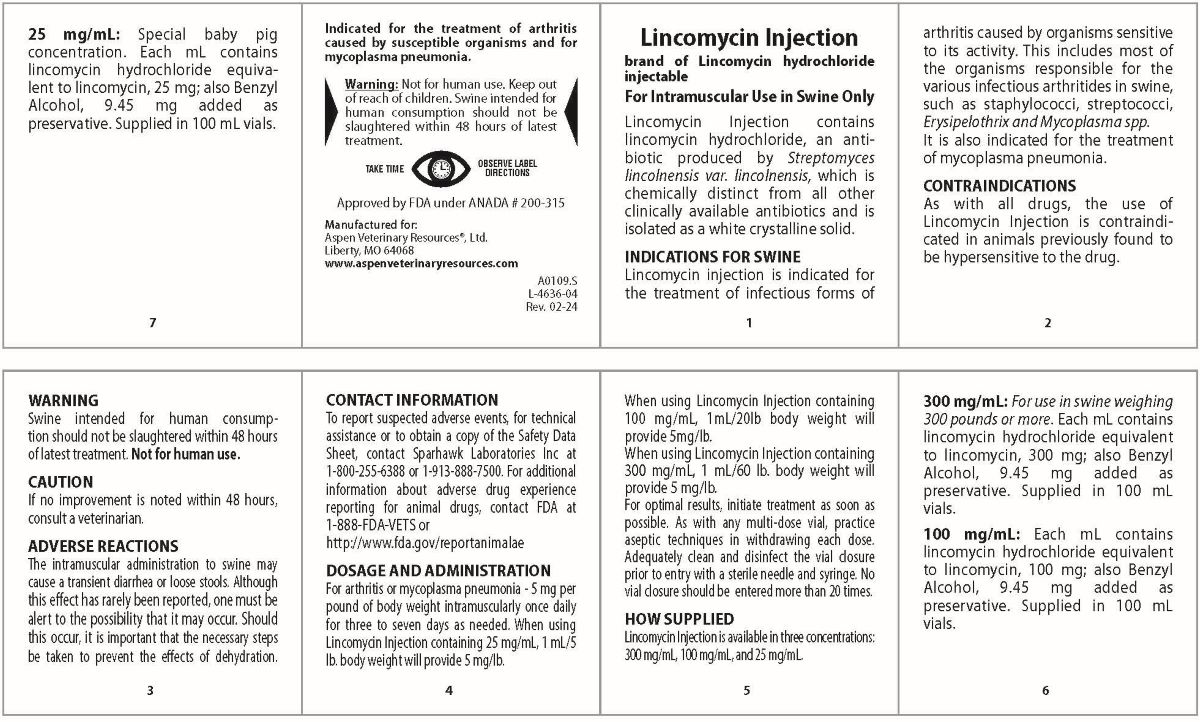 DRUG LABEL: LINCOMYCIN 
NDC: 46066-246 | Form: INJECTION
Manufacturer: Aspen Veterinary Resources, Ltd.
Category: animal | Type: OTC ANIMAL DRUG LABEL
Date: 20240320

ACTIVE INGREDIENTS: LINCOMYCIN HYDROCHLORIDE 300 mg/1 mL

LINCOMYCIN 300 INJECTION

DESCRIPTION

Sterile Lincomycin Hydrochloride Injection

Swine Antibiotic

300 mg/mL

Caution: Federal law restricts this drug to use by or on the order of a licensed veterinarian.

Not for Use in Humans
Keep out of reach of children

Approved by FDA under ANADA # 200-315

NET CONTENTS:

3.38 fl oz (100 mL)

For Intramuscular Use in Swine
Over 300 lbs. Restricted Drug - Use
Only As Directed (California).
For Use in Animals Only.

Lincomycin Injectable brand of Lincomycin hydrochloride injectable

For Intramuscular Use in Swine Only

Lincomycin Injectable contains lincomycin hydrochloride, an antibiotic produced by Streptomyces lincolnensis var. lincolnensis, which is chemically distinct from all other clinically available antibiotics and is isolated as a white crystalline solid.

INDICATIONS FOR SWINE

Lincomycin Injectable is indcated fot he treatmen of infectious forms of arthritis caused by organisms sensitive to its activity. This includes most of the organisms responsible for the various infectious arthritides in swine, such as staphylococci, streptococci, Erysipelothrix and Mycoplasma ssp.

It is also indicated for the treatment of mycoplasma pneumonia.

CONTRAINDICATIONS

As with all drugs, the use of Lincomycin Injectable is contraindicated in animals previously found to be hypersensitive to the drug.

WARNING

Swine intended for human consumption should not be slaughtered within 48 hours of latest treatment. Not for human use.

CAUTION

If no improvement is noted within 48 hours, consult a veterinarian.

ADVERSE REACTIONS

The intramuscular administration to swine may cause a transient diarrhea or loose stools. Although this effect has rarely been reported, one must be alert to the possibility that it may occur. Should this occur, it is important that the necessary steps be taken to prevent the effects of dehydration.

CONTACT INFORMATION

To report suspected adverse events, for technical assistance or to obtain a copy of the Safety Data Sheet, contact Sparhawk Laboratories Inc at 1-800-255-6388 or 1-913-888-7500. For additional information about adverse drug experience reporting for animal drugs, contact FDA at 1-888-FDA-VETS or http://www.fda.gov/reportanimalae

HOW SUPPLIED

Lincomycin Injectable is available in three concentrations: 300 mg/mL, 100 mg/mL and 25 mg/mL.

300 mg/mL: For use in swine weighing 300 pounds or more. Each mL contains lincomycin hydrochloride equivalent to lincomycin, 300 mg; also Benzyl Alcohol, 9.45 mg added as preservative. Supplied in 100 mL vials.

100 mg/mL: Each mL contains lincomycin hydrochloride equivalent to lincomycin , 100 mg; also Benzyl Alcohol, 9.45 mg added as preservative. Supplied in 100 mL vials.

25 mg/mL: Special baby pig concentration. Each mL contains lincomycin hydrochloride equivalent to lincomycin, 25 mg; also Benzyl Alcohol, 9.45 mg added as preservative. Supplied in 100 mL vials.

WARNINGS

Indicated for the treatment of arthritis caused by susceptible organisms and for mycoplasma pneumonia.

Warning: Not for human use. Keep out of reach of children. Swine intended for human consumption shold not be slaughtered within 48 hours of latest treatment.

DOSAGE

For Intramuscular Use in Swine Over 300 lbs.

For Use in Animals Only.

Usual daily dose for arthritis or mycoplasma pneumonia - 5 mg per pound of body weight (1 mL per each 60 pounds of body weight) intramuscularly for three to seven days. See package insert for ocmplete product information.

DOSAGE AND ADMINISTRATION For arthritis or mycoplasma pneumonia - 5 mg per pound of body weight intramuscularly once daily for three to seven days as needed. When using Lincomycin Injectable containing 25 mg/mL, 1 mL/5 lb. body weight will provide 5 mg/lb.
When using Lincomycin Injectable containing 100 mg/mL, 1mL/20lb body weight will provide 5mg/lb. When using Lincomycin Injectable containing 300 mg/mL, 1 mL/60 lb. body weight will provide 5 mg/lb. For optimal results, initiate treatment as soon as possible. As with any multi-dose vial, practice aseptic techniques in withdrawing each dose. Adequately clean and disinfect the vial closure prior to entry with a sterile needle and syringe. No vial closure should be entered more than 20 times.

Contains per mL

Lincomycin Hydrochloride equivalent to Lincomycin 300 mg; also Benzyl Alcohol, 9.45 mg added as preservative.

STORAGE AND HANDLING

Store at controlled room temperature: 20o to 25oC (68o to 77oF) [See USP]